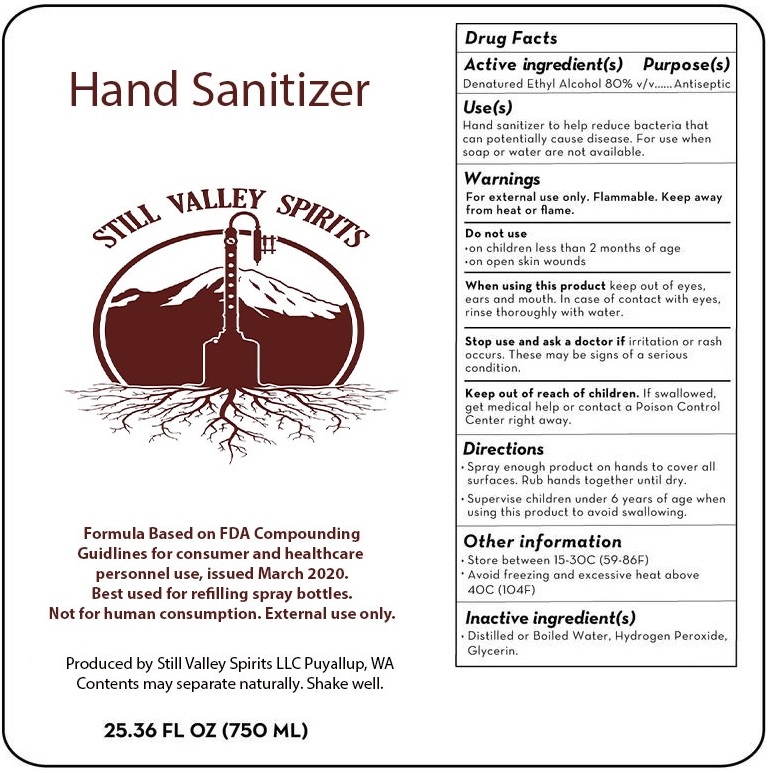 DRUG LABEL: Hand Sanitizer
NDC: 78684-080 | Form: LIQUID
Manufacturer: STILL VALLEY SPIRITS LLC
Category: otc | Type: HUMAN OTC DRUG LABEL
Date: 20200623

ACTIVE INGREDIENTS: ALCOHOL 80 mL/100 mL
INACTIVE INGREDIENTS: WATER; HYDROGEN PEROXIDE; GLYCERIN

STILL VALLEY SPIRITS Hand Sanitizer

Active ingredient(s)

Denatured Ethyl Alcohol 80% v/v

Purpose(s)

Antiseptic

Uses(s)

Hand sanitizer to help reduce bacteria that can potentially cause disease. For use when soap or water are not available.

Warnings

For external use only. Flammable. Keep away from heat or flame

Do not use

• on children less than 2 months of age

• on open skin wounds

When using this product keep out of eyes, ears, and mouth. In case of contact with eyes, rinse thoroughly with water.

Stop use and ask a doctor if irritation or rash occurs. These may be signs of a serious condition.

Keep out of reach of children. If swallowed, get medical help or contact a Poison Control Center right away.

Directions

• Spray enough product on hands to cover all surfaces. Rub hands together until dry.

• Supervise children under 6 years of age when using this product to avoid swallowing.

Other information

• Store between 15-30°C (59-86°F)

• Avoid freezing and excessive heat above 40°C (104°F)

Inactive ingredient(s)

• Distilled or Boiled Water, Hydrogen Peroxide, Glycerin

Formula Based on FDA Compounding Guidlines for consumer and healthcare personnel use, issued March 2020.

Best used for refilling spray bottles.

Not for human consumption. External use only.

Produced by Still Valley Spirits LLC Puyallup, WA

Contents may separate naturally. Shake well.